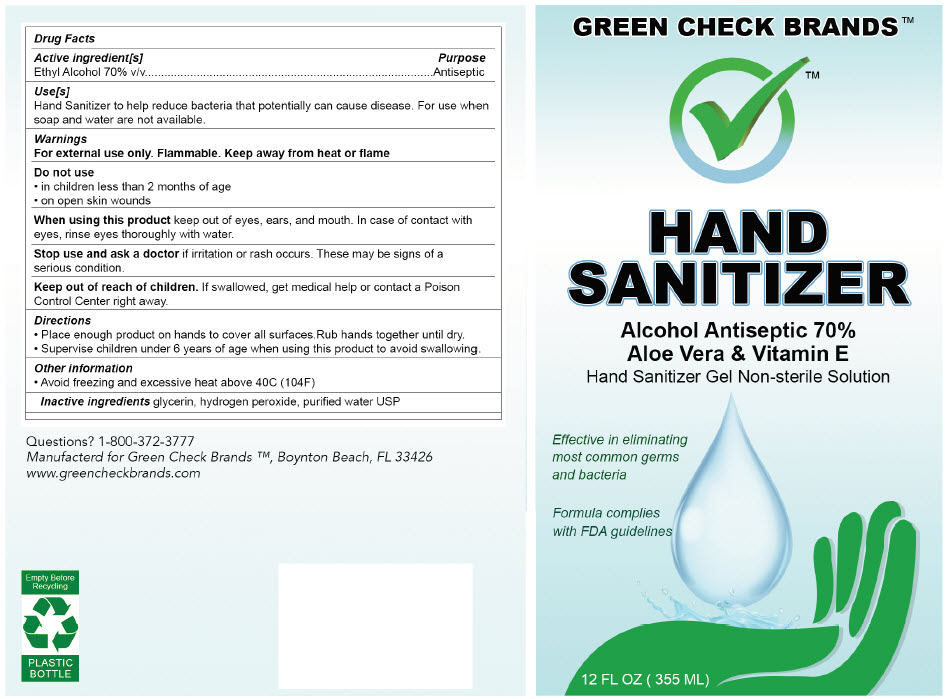 DRUG LABEL: Green Check Brands
NDC: 79756-001 | Form: GEL
Manufacturer: Green Check Brands, LLC
Category: otc | Type: HUMAN OTC DRUG LABEL
Date: 20200902

ACTIVE INGREDIENTS: Alcohol 70 mL/100 mL
INACTIVE INGREDIENTS: Water; Glycerin; Aloe; .ALPHA.-TOCOPHEROL ACETATE; Trolamine; CARBOMER HOMOPOLYMER, UNSPECIFIED TYPE

Green Check Brands™

Drug Facts

Active ingredient[s]

Ethyl Alcohol 70% v/v

Purpose

Antiseptic

Use[s]

Hand Sanitizer to help reduce bacteria that potentially can cause disease. For use when soap and water are not available.

Warnings

For external use only. Flammable. Keep away from heat or flame

Do not use

- in children less than 2 months of age
- on open skin wounds

When using this product keep out of eyes, ears, and mouth. In case of contact with eyes, rinse eyes thoroughly with water.

Stop use and ask a doctor if irritation or rash occurs. These may be signs of a serious condition.

Keep out of reach of children. If swallowed, get medical help or contact a Poison Control Center right away.

Directions

- Place enough product on hands to cover all surfaces. Rub hands together until dry.
- Supervise children under 6 years of age when using this product to avoid swallowing.

Other information

- Avoid freezing and excessive heat above 40C (104F)

Inactive ingredients

glycerin, hydrogen peroxide, purified water USP

Questions?

1-800-372-3777

PRINCIPAL DISPLAY PANEL - 355 ML Bottle Label

GREEN CHECK BRANDS™

HAND
SANITIZER

Alcohol Antiseptic 70%
Aloe Vera & Vitamin E
Hand Sanitizer Gel Non-sterile Solution

Effective in eliminating
most common germs
and bacteria

Formula complies
with FDA guidelines

12 FL OZ (355 ML)